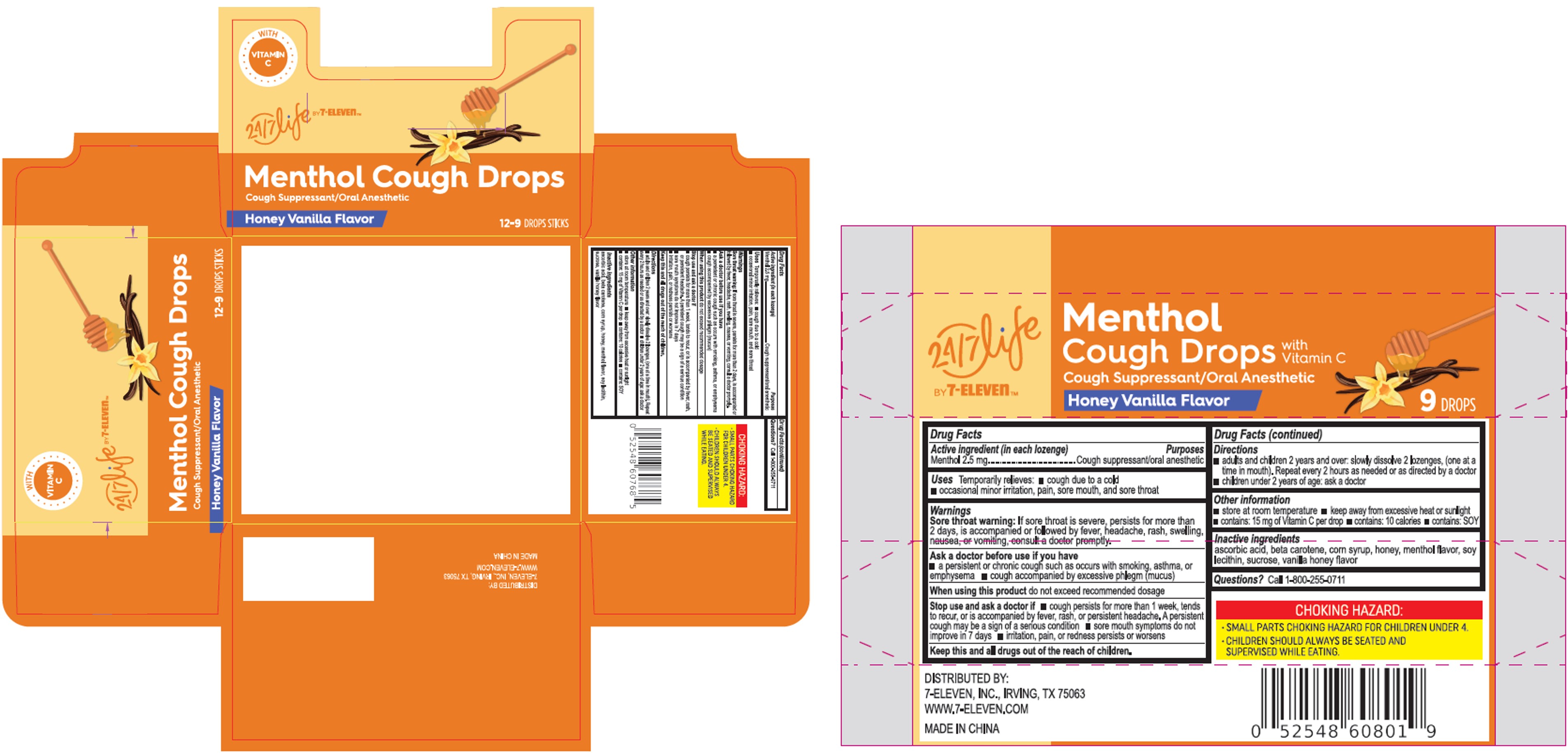 DRUG LABEL: Menthol Cough Drops Honey Vanilla Flavor
NDC: 10202-013 | Form: LOZENGE
Manufacturer: 7-ELEVEN
Category: otc | Type: HUMAN OTC DRUG LABEL
Date: 20250228

ACTIVE INGREDIENTS: MENTHOL 2.5 mg/1 1
INACTIVE INGREDIENTS: SUCROSE; ASCORBIC ACID; HONEY; CORN SYRUP; BETA CAROTENE; LECITHIN, SOYBEAN

7-Eleven MGC Xiamen VH Cough Drop

Active Ingredient (in each lozenge)

Menthol 2.5 mg

Pactin 7 mg

Purpose

Pectin: oral demulcent

Menthol: cough suppressant, oral anesthetic

Use

temporarily relieves:

- Cough due to a cold
- occasional minor irritation, pain, sore mouth, and sore throat

Warnings

Sore throat warning:If sore throat is severe, persists for more than 2 days, is accompanied or follow by fever, headache, rash, swelling, nausea, or vomiting, consult a doctor promptly.

Ask a doctor before use if you have:■ a persistent or chronic cough such as occurs with smoking, asthma, or emphysema ■ a cough accompanied by excessive phlegm (mucus).

Stop use and ask a doctor if:

- cough persists for more than 1 week, tends to recur, or is accompanied by fever, rash, or persistent headache. A persistent cough may be a sign of a serious condition
- sore mouth symptoms do not improve in 7 days
- irritation, pain, or redness persists or worsens

When using this productdo not exceed recommended dosage

KEEP OUT OF REACH OF CHILDREN

Keep this and all drugs out of the reach of children.

Directions

adults and children 2 ears and over: slowly dissolve 2 drops (one at a time in mouth). Repeat every 2 hours as needed, or as directed by a doctor

children under 2 years: ask a doctor.

Other information

- store at room temperature
- keep awar from excessive heat or sunlight
- contains: 15 mg vitamin C per drop
- contains: 10 calories per drop
- contains: SOY.

Inactive ingredients

ascorbic acid, beta carotene, corn syrup, honey, menthol flavor, soy lecithin, sucrose, vanilla honey flavor

Questions? Call 1-800-255-0711